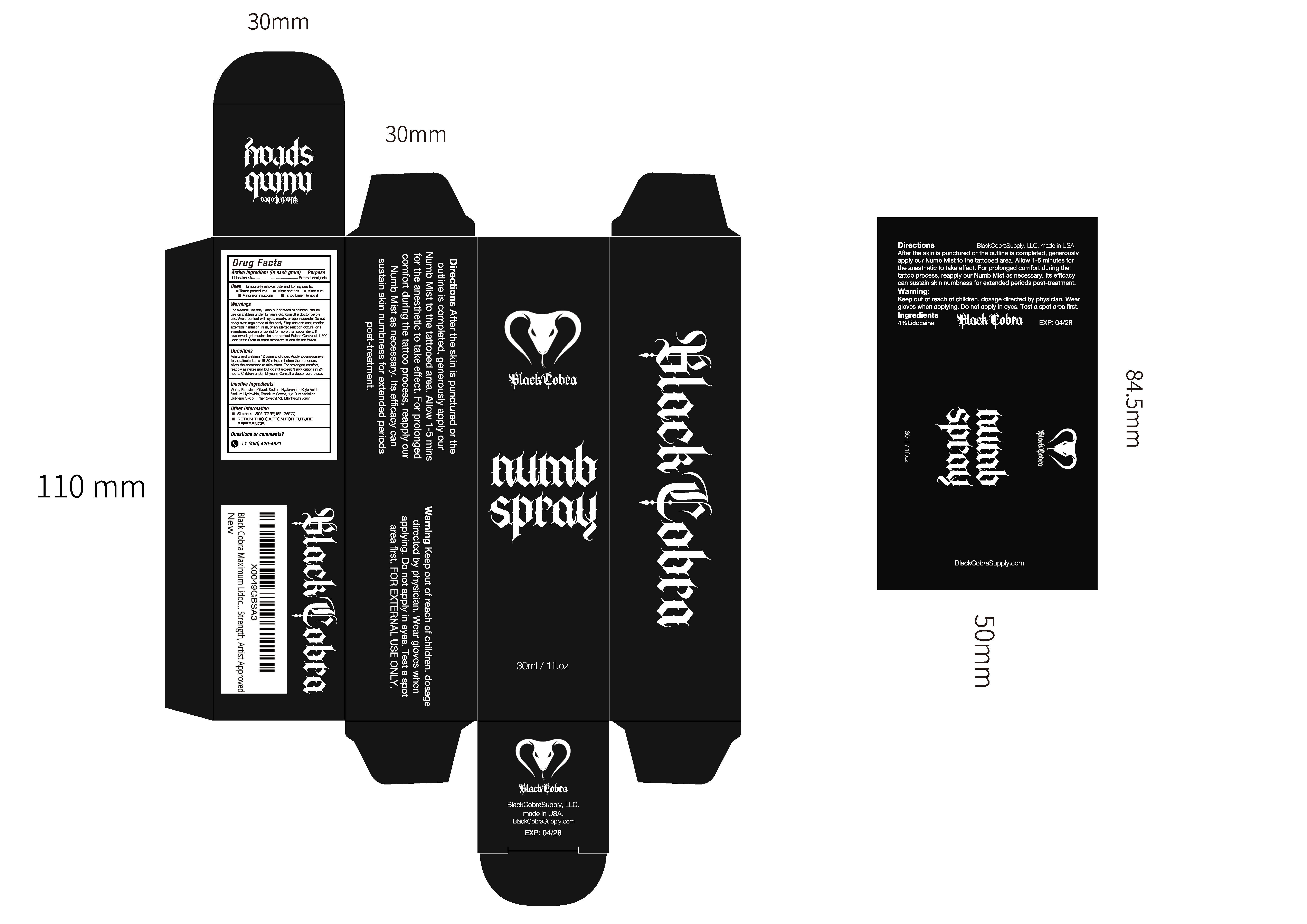 DRUG LABEL: Black Cobra Tattoo NumbingSpray 4% Lidocaine
NDC: 84938-003 | Form: LIQUID
Manufacturer: Foshan Sugar Max Cosmetics CO.,Ltd
Category: otc | Type: HUMAN OTC DRUG LABEL
Date: 20260119

ACTIVE INGREDIENTS: LIDOCAINE 0.04 g/1 mL
INACTIVE INGREDIENTS: AQUA; PHENOXYETHANOL; PROPYLENE GLYCOL; SODIUM HYDROXIDE; KOJIC ACID; BUTYLENE GLYCOL; ETHYLHEXYLGLYCERIN; SODIUM HYALURONATE; TRISODIUM CITRATE

84938-003 Black Cobra Tattoo Numbing Spray 4% Lidocaine

ACTIVE INGREDIENT

Lidocaine 4%

PURPOSE

External Analgesic

INDICATIONS AND USAGE

Temporarily relieves pain and itching due to: Tattoo procedures,
Minor scrapes, Minor cuts, Minor skin irritations,
Tattoo Laser Remova

WARNINGS

For external use only

Keep out of reach of children.
Not foruse on children under 12 years old, consult a doctor beforeuse.
Avoid contact with eyes, mouth, or open wounds.
Do not apply over large areas of the body.

Stop use and seek medicaattention if irritation, rash, or an allergic reaction occurs, or ifsymptoms worsen or persist for more than seven days.

KEEP OUT OF REACH OF CHILDREN

lf swallowed, get medical help or contact Poison Control at 1-800-222-1222.Store at room temperature and do not freeze

DOSAGE AND ADMINISTRATION

Adults and children 12 years and older: Apply a generouslayerto the affected area 15-30 minutes before the procedure.Allow the anesthetic to take effect, For prolonged comfort,reapply as necessary, but do not exceed 3 applications in 24hours. Children under 12 years: Consult a doctor before use.

INACTIVE INGREDIENT

Aqua
Propylene Glycol
Sodium Hyaluronate
Kojic Acid
Sodium Hydroxide
Trisodium Citrate
1,3-Butanediol
Phenoxyethanol
Ethylhexylglycerin